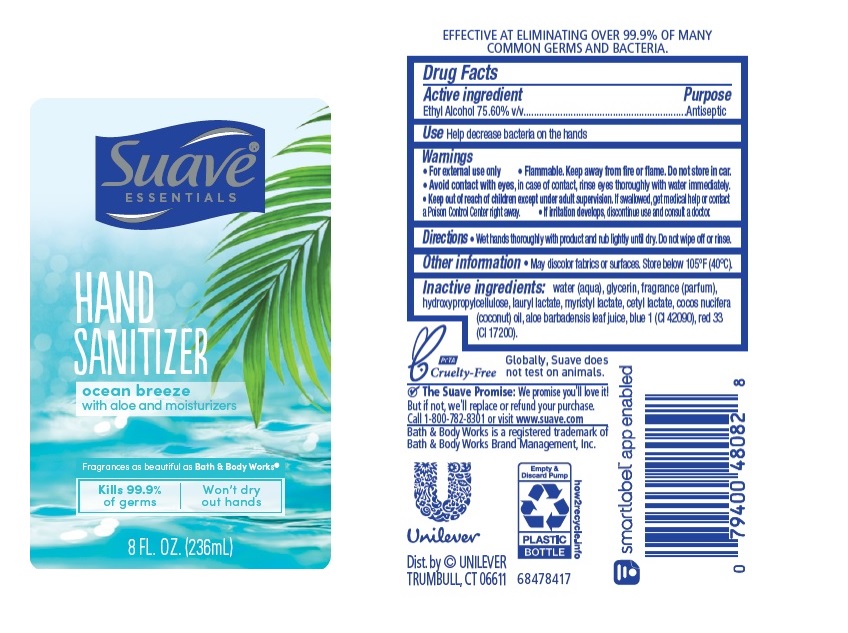 DRUG LABEL: Suave
NDC: 64942-2043 | Form: GEL
Manufacturer: Conopco Inc. d/b/a/ Unilever
Category: otc | Type: HUMAN OTC DRUG LABEL
Date: 20220831

ACTIVE INGREDIENTS: ALCOHOL 75.6 mL/100 mL
INACTIVE INGREDIENTS: HYDROXYPROPYL CELLULOSE, UNSPECIFIED; LAURYL LACTATE; MYRISTYL LACTATE; WATER; GLYCERIN; COCONUT OIL; ALOE VERA LEAF; FD&C BLUE NO. 1; D&C RED NO. 33; CETYL LACTATE

Suave Essentials Ocean Breeze Hand Sanitizer

SUAVE ESSENTIALS OCEAN BREEZE HAND SANITIZER - Ethyl Alcohol gel

Suave Skin Solutions Hand Sanitizer Lotion

Drug Facts

Active ingredient

Ethyl Alcohol 75.60%

Purpose

Antiseptic

Uses

helps decrease bacteria on the hands

Warnings

For external use only
Flammable. Keep away from fire or flame
Do not store in car.
Avoid contact with eyes, In case of contact, rinse eyes thoroughly with water.
If irritation develops, discontinue use and consult a doctor.

• Keep out of reach of children except under adult supervision.

If swallowed, get medical help or contact a poison control Center right away.

Directions

Wet hand thoroughly with product and rub lightly until dry. Do not wipe off or rinse

Other information

• May discolor fabrics or surfaces.
• Store below 105˚F (40˚C).

Inactive ingredients

Water (Aqua), Glycerin, Fragrance (Parfum), Hydroxypropylcellulose, Lauryl Lactate, Myristyl Lactate, Cetyl Lactate, Cocos Nucifera (Coconut) Oil, Aloe Barbadensis Leaf Juice, Blue 1 (CI 42090) Red 33 (CI 17200).

Call

1-800-782-8301 or visit www.suave.com